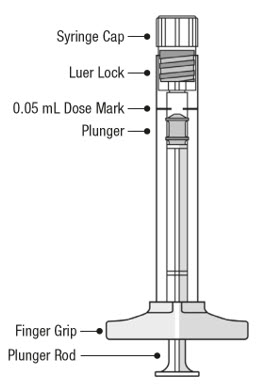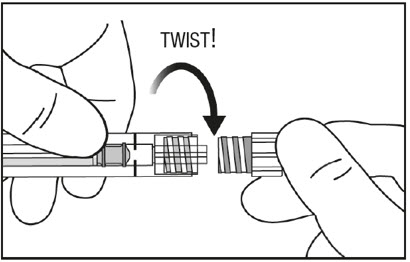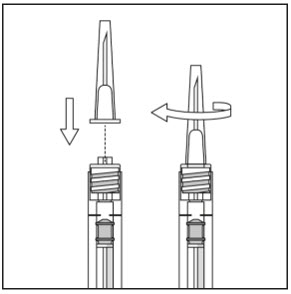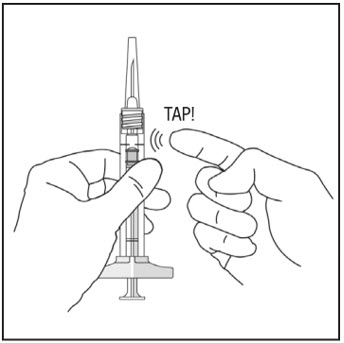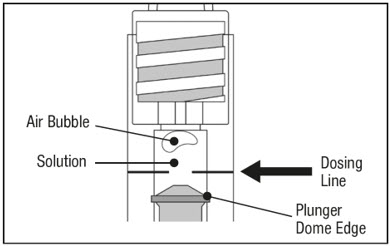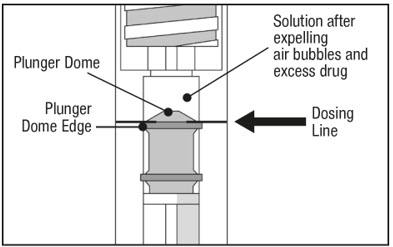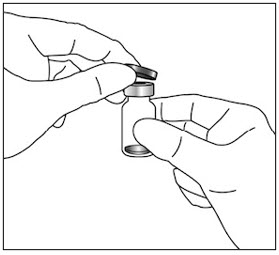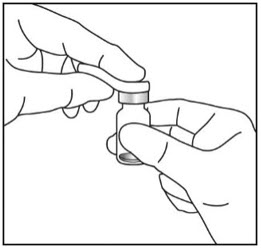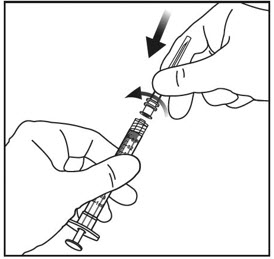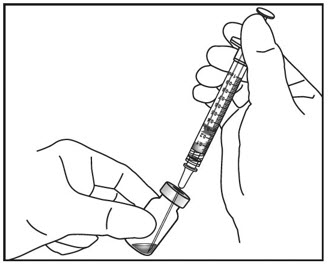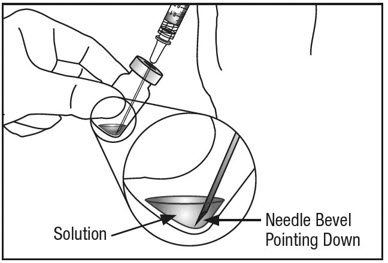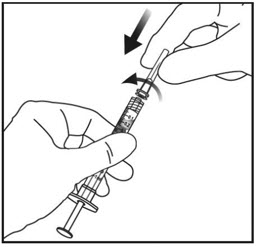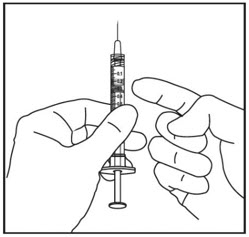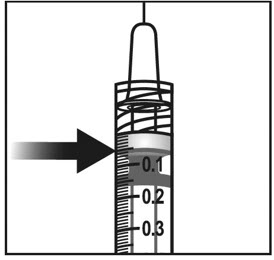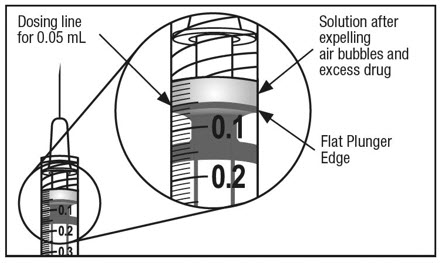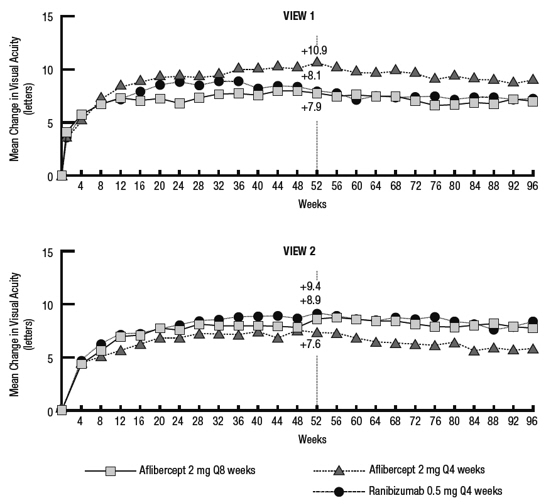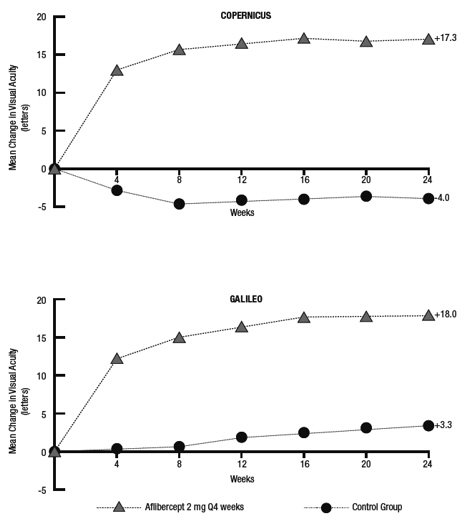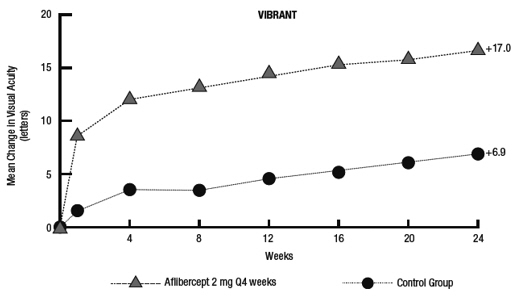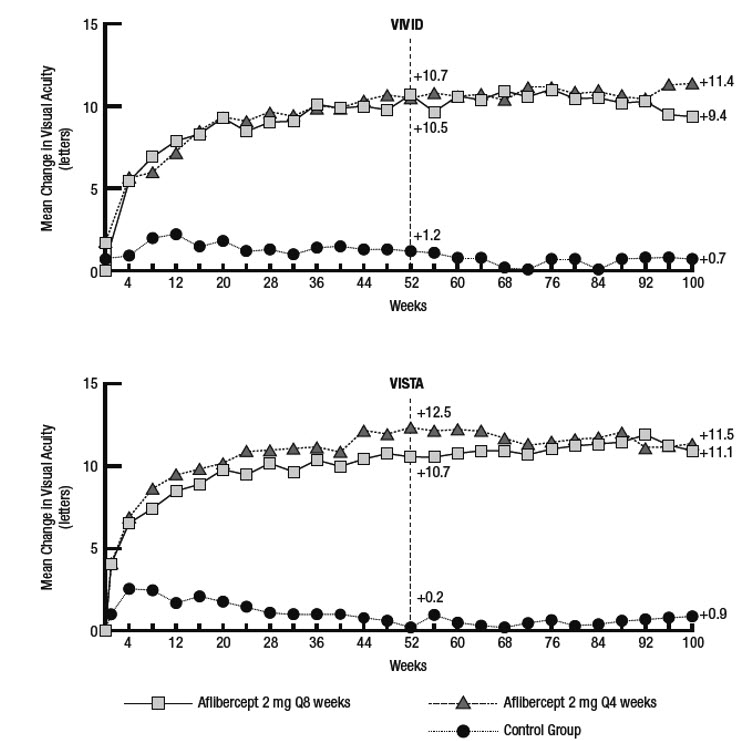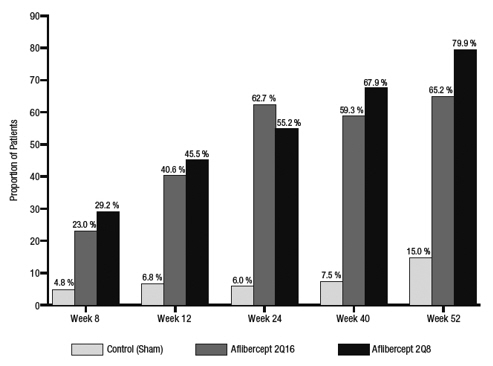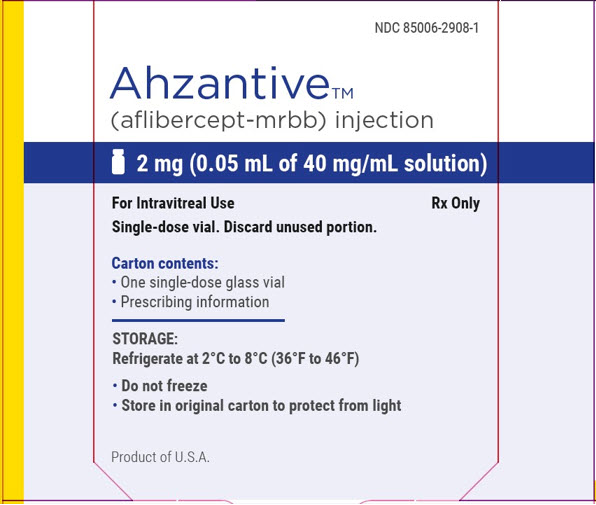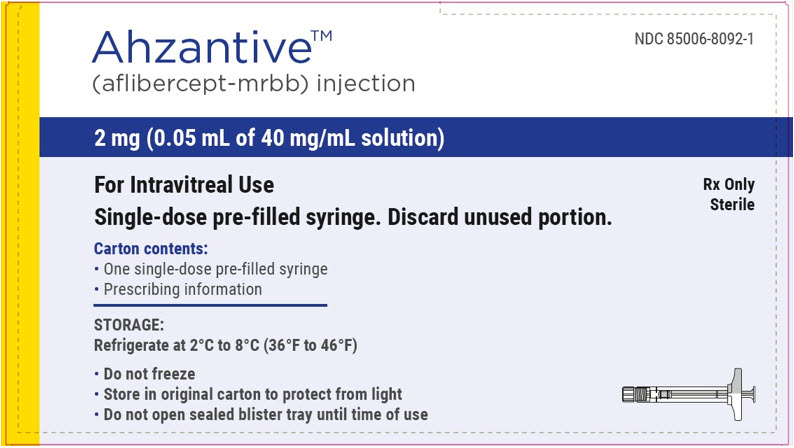 DRUG LABEL: AHZANTIVE
NDC: 85006-2908 | Form: INJECTION, SOLUTION
Manufacturer: Valorum Biologics, LLC
Category: prescription | Type: HUMAN PRESCRIPTION DRUG LABEL
Date: 20251027

ACTIVE INGREDIENTS: AFLIBERCEPT-MRBB 40 mg/1 mL

HIGHLIGHTS OF PRESCRIBING INFORMATION

These highlights do not include all the information needed to use AHZANTIVE safely and effectively. See full prescribing information for AHZANTIVE. Initial U.S. Approval: 2024

These highlights do not include all the information needed to use AHZANTIVE safely and effectively. See full prescribing information for AHZANTIVE. Initial U.S. Approval: 2024

AHZANTIVE is a vascular endothelial growth factor (VEGF) inhibitor indicated for the treatment of patients with:

- Neovascular (Wet) Age-Related Macular Degeneration (AMD) (1.1)
- Macular Edema Following Retinal Vein Occlusion (RVO) (1.2)
- Diabetic Macular Edema (DME) (1.3)
- Diabetic Retinopathy (DR) (1.4)

- Neovascular (Wet) Age-Related Macular Degeneration (AMD)
- The recommended dose for AHZANTIVE is 2 mg (0.05 mL of 40 mg/mL solution) administered by intravitreal injection every 4 weeks (approximately every 28 days, monthly) for the first 3 months, followed by 2 mg (0.05 mL of 40 mg/mL solution) via intravitreal injection once every 8 weeks (2 months). (2 .2)
- Although AHZANTIVE may be dosed as frequently as 2 mg every 4 weeks (approximately every 25 days, monthly), additional efficacy was not demonstrated in most patients when aflibercept was dosed every 4 weeks compared to every 8 weeks. Some patients may need every 4 week (monthly) dosing after the first 12 weeks (3 months). (2 .2)
- Although not as effective as the recommended every 8 week dosing regimen, patients may also be treated with one dose every 12 weeks after one year of effective therapy. Patients should be assessed regularly. (2.2)
- Macular Edema Following Retinal Vein Occlusion (RVO)
- The recommended dose for AHZANTIVE is 2 mg (0.05 mL of 40 mg/mL solution) administered by intravitreal injection once every 4 weeks (approximately every 25 days, monthly). (2.3)
- Diabetic Macular Edema (DME) and Diabetic Retinopathy (DR)
- The recommended dose for AHZANTIVE is 2 mg (0.05 mL of 40 mg/mL solution) administered by intravitreal injection every 4 weeks (approximately every 28 days, monthly) for the first 5 injections followed by 2 mg (0.05 mL of 40 mg/mL solution) via intravitreal injection once every 8 weeks (2 months). (2.4, 2.5)
- Although AHZANTIVE may be dosed as frequently as 2 mg every 4 weeks (approximately every 25 days, monthly), additional efficacy was not demonstrated in most patients when aflibercept was dosed every 4 weeks compared to every 8 weeks. Some patients may need every 4 week (monthly) dosing after the first 20 weeks (5 months). (2.4, 2.5)

Injection: 2 mg (0.05 mL of 40 mg/mL) solution in a single-dose pre-filled syringe (3)

Injection: 2 mg (0.05 mL of 40 mg/mL) solution in a single-dose vial (3)

- Ocular or periocular infections (4.1)
- Active intraocular inflammation (4.2)
- Hypersensitivity (4.3)

- Endophthalmitis, retinal detachments, and retinal vasculitis with or without occlusion may occur following intravitreal injections. Patients and/or caregivers should be instructed to report any signs and/or symptoms suggestive of endophthalmitis, retinal detachment or retinal vasculitis without delay and should be managed appropriately. (5.1)
- Increases in intraocular pressure have been seen within 60 minutes of an intravitreal injection. (5.2)
- There is a potential risk of arterial thromboembolic events following intravitreal use of VEGF inhibitors. (5.3)

The most common adverse reactions (≥5%) reported in patients receiving aflibercept were conjunctival hemorrhage, eye pain, cataract, vitreous detachment, vitreous floaters, and intraocular pressure increased. (6.1)

To report SUSPECTED ADVERSE REACTIONS, contact Formycon at 1-800-387-2746 or FDA at 1-800-FDA-1088 or www.fda.gov/medwatch.

See 17 for PATIENT COUNSELING INFORMATION.

RECENT MAJOR CHANGES

Dosage and Administration (2.1, 2.6, 2.8) 4/2025

FULL PRESCRIBING INFORMATION

These highlights do not include all the information needed to use AHZANTIVE safely and effectively. See full prescribing information for AHZANTIVE. Initial U.S. Approval: 2024

1 INDICATIONS AND USAGE

AHZANTIVE is indicated for the treatment of:

1.1 Neovascular (Wet) Age-Related Macular Degeneration (AMD)
1.2 Macular Edema Following Retinal Vein Occlusion (RVO)
1.3 Diabetic Macular Edema (DME)
1.4 Diabetic Retinopathy (DR)

2. DOSAGE AND ADMINISTRATION

2.1 Important Injection Instructions

For ophthalmic intravitreal injection. AHZANTIVE must only be administered by a qualified physician.

Pre-filled Syringe: A 30-gauge × ½-inch sterile injection needle is needed but not provided.

Vial: A 5-micron sterile filter needle (18-gauge × 1½-inch), a 1-mL sterile Luer lock syringe and a 30‑gauge × ½-inch sterile injection needle are needed, but not provided.

AHZANTIVE is available packaged as follows:

- Pre-filled Syringe. The AHZANTIVE pre-filled syringe cap and plunger are not made with natural rubber latex.
- Vial Only. The AHZANTIVE vial stopper is not made with natural rubber latex.

[see How Supplied/Storage and Handling (16)].

2.2 Neovascular (Wet) Age-Related Macular Degeneration (AMD)

The recommended dose for AHZANTIVE is 2 mg (0.05 mL of 40 mg/mL solution) administered by intravitreal injection every 4 weeks (approximately every 28 days, monthly) for the first 12 weeks (3 months), followed by 2 mg (0.05 mL of 40 mg/mL solution) via intravitreal injection once every 8 weeks (2 months). Although AHZANTIVE may be dosed as frequently as 2 mg every 4 weeks (approximately every 25 days, monthly), additional efficacy was not demonstrated in most patients when aflibercept was dosed every 4 weeks compared to every 8 weeks [see Clinical Studies (14.1)]. Some patients may need every 4 week (monthly) dosing after the first 12 weeks (3 months). Although not as effective as the recommended every 8 week dosing regimen, patients may also be treated with one dose every 12 weeks after one year of effective therapy. Patients should be assessed regularly.

2.3 Macular Edema Following Retinal Vein Occlusion (RVO)

The recommended dose for AHZANTIVE is 2 mg (0.05 mL of 40 mg/mL solution) administered by intravitreal injection once every 4 weeks (approximately every 25 days, monthly) [see Clinical Studies (14.2), (14.3)].

2.4 Diabetic Macular Edema (DME)

The recommended dose for AHZANTIVE is 2 mg (0.05 mL of 40 mg/mL solution) administered by intravitreal injection every 4 weeks (approximately every 28 days, monthly) for the first 5 injections, followed by 2 mg (0.05 mL of 40 mg/mL solution) via intravitreal injection once every 8 weeks (2 months). Although AHZANTIVE may be dosed as frequently as 2 mg every 4 weeks (approximately every 25 days, monthly), additional efficacy was not demonstrated in most patients when aflibercept was dosed every 4 weeks compared to every 8 weeks [see Clinical Studies (14.4)]. Some patients may need every 4 week (monthly) dosing after the first 20 weeks
(5 months).

2.5 Diabetic Retinopathy (DR)

The recommended dose for AHZANTIVE is 2 mg (0.05 mL of 40 mg/mL solution) administered by intravitreal injection every 4 weeks (approximately every 28 days, monthly) for the first 5 injections, followed by 2 mg (0.05 mL of 40 mg/mL solution) via intravitreal injection once every 8 weeks (2 months). Although AHZANTIVE may be dosed as frequently as 2 mg every 4 weeks (approximately every 25 days, monthly), additional efficacy was not demonstrated in most patients when aflibercept was dosed every 4 weeks compared to every 8 weeks [see Clinical Studies (14.5)]. Some patients may need every 4 week (monthly) dosing after the first 20 weeks (5 months).

2.6 Preparation for Administration - Pre-filled Syringe

The AHZANTIVE pre-filled syringe is sterile and for one-time use in one eye only.

The pre-filled syringe should be inspected visually prior to administration. Do not use if particulates, cloudiness, or discoloration are visible, or if the package is open or damaged.

Do not use if any part of the pre-filled syringe is damaged or if the syringe cap is detached from the Luer lock.

The intravitreal injection should be performed with a 30-gauge x ½-inch injection needle (not provided).

The pre-filled syringe contains more than the recommended dose of 2 mg aflibercept-mrbb (equivalent to 50 microliters). The excess volume must be discarded prior to the administration.

PRE-FILLED SYRINGE DESCRIPTION - Figure 1:

Use aseptic technique to carry out the following steps:

1. PREPARE

When ready to administer AHZANTIVE, open the carton and remove sterilized blister pack. Carefully peel open the sterilized blister pack ensuring the sterility of its contents. Keep the syringe in the sterile tray until you are ready for assembly.

2. REMOVE SYRINGE

Using aseptic technique, remove the syringe from the sterilized blister pack.

3. TWIST OFF SYRINGE CAP

Twist off (do not snap off) the syringe cap by holding the syringe in one hand and the syringe cap with the thumb and forefinger of the other hand (see Figure 2).

Figure 2:

4. ATTACH NEEDLE

Using aseptic technique, firmly twist a 30-gauge x ½-inch injection needle onto the Luer lock syringe tip (see Figure 3).

Figure 3:

Note: When ready to administer AHZANTIVE, remove the plastic needle shield from the needle.

5. DISLODGE AIR BUBBLES

Holding the syringe with the needle pointing up, check the syringe for bubbles. If there are bubbles, gently tap the syringe with your finger until the bubbles rise to the top (see Figure 4).

Figure 4:

6. EXPEL AIR AND SET THE DOSE

To eliminate all bubbles and to expel excess drug, slowly depress the plunger rod to align the plunger dome edge (see Figure 5a) with the black dosing line on the syringe (equivalent to 50 microliters) (see Figure 5b).

Figure 5a:

Figure 5b:

7. The pre-filled syringe is for one-time use in one eye only. After injection any unused product must be discarded.

2.7 Preparation for Administration - Vial

AHZANTIVE should be inspected visually prior to administration. If particulates, cloudiness, or discoloration are visible, the vial must not be used.

The glass vial is for one-time use in one eye only. Discard unused portion.

Use aseptic technique to carry out the following preparation steps:

Prepare for intravitreal injection with the following medical devices for single use (not provided):

- a 5-micron sterile filter needle (18-gauge × 1½-inch)
- a 1-mL sterile Luer lock syringe (with marking to measure 0.05 mL)
- a sterile injection needle (30-gauge × ½-inch)

1. Remove the protective plastic cap from the vial (see Figure 6).

Figure 6:

2. Clean the top of the vial with an alcohol wipe (see Figure 7).

Figure 7:

3. Remove the 18-gauge x 1½-inch, 5-micron, filter needle and the 1-mL syringe from their packaging. Attach the filter needle to the syringe by twisting it onto the Luer lock syringe tip (see Figure 8).

Figure 8:

4. Push the filter needle into the center of the vial stopper until the needle is completely inserted into the vial and the tip touches the bottom or bottom edge of the vial.

5. Using aseptic technique withdraw all of the AHZANTIVE vial contents into the syringe, keeping the vial in an upright position, slightly inclined to ease complete withdrawal. To deter the introduction of air, ensure the bevel of the filter needle is submerged into the liquid. Continue to tilt the vial during withdrawal keeping the bevel of the filter needle submerged in the liquid (see Figure 9a and Figure 9b).

Figure 9a:

Figure 9b:

6. Ensure that the plunger rod is drawn sufficiently back when emptying the vial in order to completely empty the filter needle.

7. Remove the filter needle from the syringe and properly dispose of the filter needle.
Note: Filter needle is not to be used for intravitreal injection.

8. Remove the 30-gauge x ½-inch injection needle from its packaging and attach the injection needle to the syringe by firmly twisting the injection needle onto the Luer lock syringe tip (see Figure 10).

Figure 10:

9. When ready to administer AHZANTIVE, remove the plastic needle shield from the needle.

10. Holding the syringe with the needle pointing up, check the syringe for bubbles. If there are bubbles, gently tap the syringe with your finger until the bubbles rise to the top (see Figure 11).

Figure 11:

11. To eliminate all of the bubbles and to expel excess drug, SLOWLY depress the plunger rod so that the plunger edge aligns with the line that marks 0.05 mL on the syringe (see Figure 12a and Figure 12b).

Figure 12a:

Figure 12b:

2.8 Injection Procedure

The intravitreal injection procedure should be carried out under controlled aseptic conditions, which include surgical hand disinfection and the use of sterile gloves, a sterile drape, and a sterile eyelid speculum (or equivalent). Adequate anesthesia and a topical broad–spectrum microbicide should be given prior to the injection.

Pre-filled syringe: Inject by pressing the plunger carefully and with constant pressure. Do not apply additional pressure once the plunger has reached the bottom of the syringe. A small residual volume may remain in the syringe after a full dose has been injected. This is normal. Do not administer any residual solution observed in the syringe.

Immediately following the intravitreal injection, patients should be monitored for elevation in intraocular pressure. Appropriate monitoring may consist of a check for perfusion of the optic nerve head or tonometry. If required, a sterile paracentesis needle should be available.

Following intravitreal injection, patients and/or caregivers should be instructed to report any signs and/or symptoms suggestive of endophthalmitis or retinal detachment (e.g., eye pain, redness of the eye, photophobia, blurring of vision) without delay [see Patient Counseling Information (17)].

Each sterile vial should only be used for the treatment of a single eye. If the contralateral eye requires treatment, a new sterile vial should be used and the sterile field, syringe, gloves, drapes, eyelid speculum, filter, and injection needles should be changed before AHZANTIVE is administered to the other eye.

After injection, any unused product must be discarded.

3. DOSAGE FORMS AND STRENGTHS

AHZANTIVE is a clear, colorless to pale yellow solution available as:

- Injection: 2 mg (0.05 mL of a 40 mg/mL solution) in a single-dose pre-filled syringe
- Injection: 2 mg (0.05 mL of a 40 mg/mL solution) in a single-dose glass vial

4. CONTRAINDICATIONS

4.1 Ocular or Periocular Infections

AHZANTIVE is contraindicated in patients with ocular or periocular infections.

4.2 Active Intraocular Inflammation

AHZANTIVE is contraindicated in patients with active intraocular inflammation.

4.3 Hypersensitivity

AHZANTIVE is contraindicated in patients with known hypersensitivity to aflibercept or any of the excipients in AHZANTIVE. Hypersensitivity reactions may manifest as rash, pruritus, urticaria, severe anaphylactic/anaphylactoid reactions, or severe intraocular inflammation.

5. WARNINGS AND PRECAUTIONS

5.1 Endophthalmitis, Retinal Detachments, and Retinal Vasculitis with or without Occlusion

Intravitreal injections, including those with aflibercept products, have been associated with endophthalmitis and retinal detachments [see Adverse Reactions (6.1)] and, more rarely, retinal vasculitis with or without occlusion [see Adverse Reactions (6.2)]. Proper aseptic injection technique must always be used when administering AHZANTIVE. Patients and/or caregivers should be instructed to report any signs and/or symptoms suggestive of endophthalmitis, retinal detachment, or retinal vasculitis without delay and should be managed appropriately [see Dosage and Administration (2.7) and Patient Counseling Information (17)].

5.2 Increase in Intraocular Pressure

Acute increases in intraocular pressure have been seen within 60 minutes of intravitreal injection, including with aflibercept products [see Adverse Reactions (6.1)]. Sustained increases in intraocular pressure have also been reported after repeated intravitreal dosing with vascular endothelial growth factor (VEGF) inhibitors. Intraocular pressure and the perfusion of the optic nerve head should be monitored and managed appropriately [see Dosage and Administration (2.7)].

5.3 Thromboembolic Events

There is a potential risk of arterial thromboembolic events (ATEs) following intravitreal use of VEGF inhibitors, including aflibercept products. ATEs are defined as nonfatal stroke, nonfatal myocardial infarction, or vascular death (including deaths of unknown cause). The incidence of reported thromboembolic events in wet AMD studies during the first year was 1.8% (32 out of 1824) in the combined group of patients treated with aflibercept compared with 1.5% (9 out of 595) in patients treated with ranibizumab; through 96 weeks, the incidence was 3.3% (60 out of 1824) in the aflibercept group compared with 3.2% (19 out of 595) in the ranibizumab group. The incidence in the DME studies from baseline to week 52 was 3.3% (19 out of 578) in the combined group of patients treated with aflibercept compared with 2.8% (8 out of 287) in the control group; from baseline to week 100, the incidence was 6.4% (37 out of 578) in the combined group of patients treated with aflibercept compared with 4.2% (12 out of 287) in the control group. There were no reported thromboembolic events in the patients treated with aflibercept in the first six months of the RVO studies.

6 ADVERSE REACTIONS

The following potentially serious adverse reactions are described elsewhere in the labeling:

- Hypersensitivity [see Contraindications (4.3)]
- Endophthalmitis, Retinal Detachments, and Retinal Vasculitis with or without Occlusion [see Warnings and Precautions (5.1)]
- Increase in intraocular pressure [see Warnings and Precautions (5.2)]
- Thromboembolic events [see Warnings and Precautions (5.3)]

6.1 Clinical Trials Experience

Because clinical trials are conducted under widely varying conditions, adverse reaction rates observed in the clinical trials of a drug cannot be directly compared to rates in other clinical trials of the same or another drug and may not reflect the rates observed in practice.

A total of 2980 adult patients treated with aflibercept constituted the safety population in eight phase 3 studies. Among those, 2379 patients were treated with the recommended dose of 2 mg. Serious adverse reactions related to the injection procedure have occurred in <0.1% of intravitreal injections with aflibercept including endophthalmitis and retinal detachment. The most common adverse reactions (≥5%) reported in patients receiving aflibercept were conjunctival hemorrhage, eye pain, cataract, vitreous detachment, vitreous floaters, and intraocular pressure increased.

Neovascular (Wet) Age-Related Macular Degeneration (AMD)

The data described below reflect exposure to aflibercept in 1824 patients with wet AMD, including 1223 patients treated with the 2-mg dose, in 2 double-masked, controlled clinical studies (VIEW1 and VIEW2) for 24 months (with active control in year 1) [see Clinical Studies (14.1)].

Safety data observed in the aflibercept group in a 52-week, double-masked, Phase 2 study were consistent with these results.

Table 1: Most Common Adverse Reactions (≥1%) in Wet AMD Studies

Adverse Reactions | Baseline to Week 52 |  | Baseline to Week 96
Adverse Reactions | Aflibercept (N=1824) | Active Control (ranibizumab) (N=595) | Aflibercept (N=1824) | Control (ranibizumab) (N=595)
Conjunctival hemorrhage | 25% | 28% | 27% | 30%
Eye pain | 9% | 9% | 10% | 10%
Cataract | 7% | 7% | 13% | 10%
Vitreous detachment | 6% | 6% | 8% | 8%
Vitreous floaters | 6% | 7% | 8% | 10%
Intraocular pressure increased | 5% | 7% | 7% | 11%
Ocular hyperemia | 4% | 8% | 5% | 10%
Corneal epithelium defect | 4% | 5% | 5% | 6%
Detachment of the retinal pigment epithelium | 3% | 3% | 5% | 5%
Injection site pain | 3% | 3% | 3% | 4%
Foreign body sensation in eyes | 3% | 4% | 4% | 4%
Lacrimation increased | 3% | 1% | 4% | 2%
Vision blurred | 2% | 2% | 4% | 3%
Intraocular inflammation | 2% | 3% | 3% | 4%
Retinal pigment epithelium tear | 2% | 1% | 2% | 2%
Injection site hemorrhage | 1% | 2% | 2% | 2%
Eyelid edema | 1% | 2% | 2% | 3%
Corneal edema | 1% | 1% | 1% | 1%
Retinal detachment | <1% | <1% | 1% | 1%

Less common serious adverse reactions reported in <1% of the patients treated with aflibercept were hypersensitivity, retinal tear, and endophthalmitis.

Macular Edema Following Retinal Vein Occlusion (RVO)

The data described below reflect 6 months exposure to aflibercept with a monthly 2 mg dose in 218 patients following central retinal vein occlusion (CRVO) in 2 clinical studies (COPERNICUS and GALILEO) and 91 patients following branch retinal vein occlusion (BRVO) in one clinical study (VIBRANT) [see Clinical Studies (14.2), (14.3)].

Table 2: Most Common Adverse Reactions (≥1%) in RVO Studies

Adverse Reactions | CRVO |  | BRVO
Adverse Reactions | Aflibercept (N=218) | Control (N=142) | Aflibercept (N=91) | Control (N=92)
Eye pain | 13% | 5% | 4% | 5%
Conjunctival hemorrhage | 12% | 11% | 20% | 4%
Intraocular pressure increased | 8% | 6% | 2% | 0%
Corneal epithelium defect | 5% | 4% | 2% | 0%
Vitreous floaters | 5% | 1% | 1% | 0%
Ocular hyperemia | 5% | 3% | 2% | 2%
Foreign body sensation in eyes | 3% | 5% | 3% | 0%
Vitreous detachment | 3% | 4% | 2% | 0%
Lacrimation increased | 3% | 4% | 3% | 0%
Injection site pain | 3% | 1% | 1% | 0%
Vision blurred | 1% | <1% | 1% | 1%
Intraocular inflammation | 1% | 1% | 0% | 0%
Cataract | <1% | 1% | 5% | 0%
Eyelid edema | <1% | 1% | 1% | 0%

Less common adverse reactions reported in <1% of the patients treated with aflibercept in the CRVO studies were corneal edema, retinal tear, hypersensitivity, and endophthalmitis.

Diabetic Macular Edema (DME) and Diabetic Retinopathy (DR)

The data described below reflect exposure to aflibercept in 578 patients with DME treated with the 2-mg dose in 2 double-masked, controlled clinical studies (VIVID and VISTA) from baseline to week 52 and from baseline to week 100 [see Clinical Studies (14.4)].

Table 3: Most Common Adverse Reactions (≥1%) in DME Studies

Adverse Reactions | Baseline to Week 52 |  | Baseline to Week 100
Adverse Reactions | Aflibercept (N=578) | Control (N=287) | Aflibercept (N=578) | Control (N=287)
Conjunctival hemorrhage | 28% | 17% | 31% | 21%
Eye pain | 9% | 6% | 11% | 9%
Cataract | 8% | 9% | 19% | 17%
Vitreous floaters | 6% | 3% | 8% | 6%
Corneal epithelium defect | 5% | 3% | 7% | 5%
Intraocular pressure increased | 5% | 3% | 9% | 5%
Ocular hyperemia | 5% | 6% | 5% | 6%
Vitreous detachment | 3% | 3% | 8% | 6%
Foreign body sensation in eyes | 3% | 3% | 3% | 3%
Lacrimation increased | 3% | 2% | 4% | 2%
Vision blurred | 2% | 2% | 3% | 4%
Intraocular inflammation | 2% | <1% | 3% | 1%
Injection site pain | 2% | <1% | 2% | <1%
Eyelid edema | <1% | 1% | 2% | 1%

Less common adverse reactions reported in <1% of the patients treated with aflibercept were hypersensitivity, retinal detachment, retinal tear, corneal edema, and injection site hemorrhage.

Safety data observed in 269 patients with nonproliferative diabetic retinopathy (NPDR) through week 52 in the PANORAMA trial were consistent with those seen in the phase 3 VIVID and VISTA trials (see Table 3 above).

6.1 Postmarketing Experience

The following adverse reactions have been identified during postapproval use of aflibercept. Because these reactions are reported voluntarily from a population of uncertain size, it is not always possible to reliably estimate their frequency or establish a causal relationship to drug exposure.

Eye disorders: retinal vasculitis and occlusive retinal vasculitis related to intravitreal injection with aflibercept (reported at a rate of 0.6 and 0.2 per 1 million injections, respectively, based on postmarketing experience from November 2011 until November 2023).

8 USE IN SPECIFIC POPULATIONS

8.1 Pregnancy

Risk Summary

Adequate and well-controlled studies with aflibercept have not been conducted in pregnant women. Aflibercept produced adverse embryofetal effects in rabbits, including external, visceral, and skeletal malformations. A fetal No Observed Adverse Effect Level (NOAEL) was not identified. At the lowest dose shown to produce adverse embryofetal effects, systemic exposures (based on AUC for free aflibercept) were approximately 6 times higher than AUC values observed in humans after a single intravitreal treatment at the recommended clinical dose
[see Animal Data].

Animal reproduction studies are not always predictive of human response, and it is not known whether aflibercept can cause fetal harm when administered to a pregnant woman. Based on the anti-VEGF mechanism of action for aflibercept [see Clinical Pharmacology (12.1)], treatment with aflibercept may pose a risk to human embryofetal development. AHZANTIVE should be used during pregnancy only if the potential benefit justifies the potential risk to the fetus.

All pregnancies have a background risk of birth defect, loss, or other adverse outcomes. The background risk of major birth defects and miscarriage for the indicated population is unknown. In the U.S. general population, the estimated background risk of major birth defects and miscarriage in clinically recognized pregnancies is 2-4% and 15-20%, respectively.

Data

Animal Data

In two embryofetal development studies, aflibercept produced adverse embryofetal effects when administered every three days during organogenesis to pregnant rabbits at intravenous doses ≥3 mg per kg, or every six days during organogenesis at subcutaneous doses ≥0.1 mg per kg.

Adverse embryofetal effects included increased incidences of postimplantation loss and fetal malformations, including anasarca, umbilical hernia, diaphragmatic hernia, gastroschisis, cleft palate, ectrodactyly, intestinal atresia, spina bifida, encephalomeningocele, heart and major vessel defects, and skeletal malformations (fused vertebrae, sternebrae, and ribs; supernumerary vertebral arches and ribs; and incomplete ossification). The maternal No Observed Adverse Effect Level (NOAEL) in these studies was 3 mg per kg. Aflibercept produced fetal malformations at all doses assessed in rabbits and the fetal NOAEL was not identified. At the lowest dose shown to produce adverse embryofetal effects in rabbits (0.1 mg per kg), systemic exposure (AUC) of free aflibercept was approximately 6 times higher than systemic exposure (AUC) observed in adult patients after a single intravitreal dose of 2 mg.

8.2 Lactation

Risk Summary

There is no information regarding the presence of aflibercept products in human milk, the effects of the drug on the breastfed infant, or the effects of the drug on milk production/excretion. Because many drugs are excreted in human milk, and because the potential for absorption and harm to infant growth and development exists, AHZANTIVE is not recommended during breastfeeding.

The developmental and health benefits of breastfeeding should be considered along with the mother's clinical need for AHZANTIVE and any potential adverse effects on the breastfed child from AHZANTIVE.

8.3 Females and Males of Reproductive Potential

Contraception

Females of reproductive potential are advised to use effective contraception prior to the initial dose, during treatment, and for at least 3 months after the last intravitreal injection of AHZANTIVE.

Infertility

There are no data regarding the effects of aflibercept on human fertility. Aflibercept adversely affected female and male reproductive systems in cynomolgus monkeys when administered by intravenous injection at a dose approximately 1500 times higher than the systemic level observed in adult patients with an intravitreal dose of 2 mg. A No Observed Adverse Effect Level (NOAEL) was not identified. These findings were reversible within 20 weeks after cessation of treatment [see Nonclinical Toxicology (13.1)].

8.4 Pediatric Use

A pediatric assessment for AHZANTIVE demonstrates that AHZANTIVE is safe and effective for pediatric patients in an indication for which EYLEA (aflibercept) is approved. However, AHZANTIVE is not approved for such indication due to marketing exclusivity for EYLEA (aflibercept).

8.5 Geriatric Use

In the clinical studies, approximately 76% (2049/2701) of patients randomized to treatment with aflibercept were ≥65 years of age and approximately 46% (1250/2701) were ≥75 years of age. No significant differences in efficacy or safety were seen with increasing age in these studies.

10 OVERDOSAGE

Overdosing with increased injection volume may increase intraocular pressure. Therefore, in case of overdosage, intraocular pressure should be monitored and if deemed necessary by the treating physician, adequate treatment should be initiated.

11 DESCRIPTION

Aflibercept-mrbb is a recombinant fusion protein consisting of portions of human VEGF receptors 1 and 2 extracellular domains fused to the Fc portion of human IgG1 formulated as an iso-osmotic solution for intravitreal administration. Aflibercept-mrbb is a dimeric glycoprotein with a protein molecular weight of 97 kilodaltons (kDa) and contains glycosylation, constituting an additional 15% of the total molecular mass, resulting in a total molecular weight of 115 kDa. Aflibercept-mrbb is produced in recombinant Chinese hamster ovary (CHO) cells.

AHZANTIVE (aflibercept-mrbb) injection is a sterile, clear, and colorless to pale yellow solution. AHZANTIVE does not contain anti-microbial preservative and is supplied as a sterile, aqueous solution for intravitreal injection in a single-dose glass vial designed to deliver 0.05 mL (50 microliters) of solution containing 2 mg of aflibercept-mrbb in histidine (0.046 mg), L‑histidine hydrochloride monohydrate (0.043 mg), polysorbate 20 (0.015 mg), sodium chloride (0.117 mg), sucrose (2.5 mg) and water for injection with a pH of 6.2.

12 CLINICAL PHARMACOLOGY

12.1 Mechanism of Action

Vascular endothelial growth factor-A (VEGF-A) and placental growth factor (PlGF) are members of the VEGF family of angiogenic factors that can act as mitogenic, chemotactic, and vascular permeability factors for endothelial cells. VEGF acts via two receptor tyrosine kinases, VEGFR-1 and VEGFR-2, present on the surface of endothelial cells. PlGF binds only to VEGFR-1, which is also present on the surface of leucocytes. Activation of these receptors by VEGF-A can result in neovascularization and vascular permeability.

Aflibercept products act as soluble decoy receptors that bind VEGF-A and PlGF, and thereby can inhibit the binding and activation of these cognate VEGF receptors.

12.2 Pharmacodynamics

Neovascular (Wet) Age-Related Macular Degeneration (AMD)

In the clinical studies anatomic measures of disease activity improved similarly in all treatment groups from baseline to week 52. Anatomic data were not used to influence treatment decisions during the first year.

Macular Edema Following Retinal Vein Occlusion (RVO)

Reductions in mean retinal thickness were observed in COPERNICUS, GALILEO, and VIBRANT at week 24 compared to baseline. Anatomic data were not used to influence treatment decisions [see Clinical Studies (14.2), (14.3)].

Diabetic Macular Edema (DME)

Reductions in mean retinal thickness were observed in VIVID and VISTA at weeks 52 and 100 compared to baseline. Anatomic data were not used to influence aflibercept treatment decisions [see Clinical Studies (14.4)].

12.3 Pharmacokinetics

Aflibercept is administered intravitreally to exert local effects in the eye. In patients with wet AMD, RVO, or DME, following intravitreal administration of aflibercept, a fraction of the administered dose is expected to bind with endogenous VEGF in the eye to form an inactive aflibercept: VEGF complex. Once absorbed into the systemic circulation, aflibercept presents in the plasma as free aflibercept (unbound to VEGF) and a more predominant stable inactive form with circulating endogenous VEGF (i.e., aflibercept: VEGF complex).

Absorption/Distribution

Following intravitreal administration of 2 mg per eye of aflibercept to patients with wet AMD, RVO, and DME, the mean Cmax of free aflibercept in the plasma was 0.02 mcg/mL (range: 0 to 0.054 mcg/mL), 0.05 mcg/mL (range: 0 to 0.081 mcg/mL), and 0.03 mcg/mL (range: 0 to 0.076 mcg/mL), respectively and was attained in 1 to 3 days. The free aflibercept plasma concentrations were undetectable two weeks post-dosing in all patients. Aflibercept did not accumulate in plasma when administered as repeated doses intravitreally every 4 weeks. It is estimated that after intravitreal administration of 2 mg to patients, the mean maximum plasma concentration of free aflibercept is more than 100 fold lower than the concentration of aflibercept required to half-maximally bind systemic VEGF.

The volume of distribution of free aflibercept following intravenous (I.V.) administration of aflibercept has been determined to be approximately 6L.

Metabolism/Elimination

Aflibercept is a therapeutic protein and no drug metabolism studies have been conducted. Aflibercept is expected to undergo elimination through both target-mediated disposition via binding to free endogenous VEGF and metabolism via proteolysis. The terminal elimination half-life (t1/2) of free aflibercept in plasma was approximately 5 to 6 days after I.V. administration of doses of 2 to 4 mg/kg aflibercept.

Specific Populations

Renal Impairment

Pharmacokinetic analysis of a subgroup of patients (n=492) in one wet AMD study, of which 43% had renal impairment (mild n=120, moderate n=74, and severe n=16), revealed no differences with respect to plasma concentrations of free aflibercept after intravitreal administration every 4 or 8 weeks. Similar results were seen in patients in a RVO study and in patients in a DME study. No dose adjustment based on renal impairment status is needed for either wet AMD, RVO, or DME patients.

Other

No dosage modification is required based on gender or in the elderly.

12.6 Immunogenicity

The observed incidence of anti-drug antibodies is highly dependent on the sensitivity and specificity of the assay. Differences in assay methods preclude meaningful comparisons of the incidence of anti-drug antibodies in the studies described below with the incidence of anti-drug antibodies in other studies, including those of aflibercept or of other aflibercept products.

In the wet AMD, RVO, and DME studies, the pre-treatment incidence of immunoreactivity to aflibercept was approximately 1% to 3% across treatment groups. After dosing with aflibercept for 24-100 weeks, antibodies to aflibercept were detected in a similar percentage range of patients.

There were no differences in efficacy or safety between patients with or without immunoreactivity.

12 NONCLINICAL TOXICOLOGY

13.1 Carcinogenesis, Mutagenesis, Impairment of Fertility

No studies have been conducted on the mutagenic or carcinogenic potential of afliberceptproducts . Effects on male and female fertility were assessed as part of a 6-month study in monkeys with intravenous administration of aflibercept at weekly doses ranging from 3 to 30 mg per kg.

Absent or irregular menses associated with alterations in female reproductive hormone levels and changes in sperm morphology and motility were observed at all dose levels. In addition, females showed decreased ovarian and uterine weight accompanied by compromised luteal development and reduction of maturing follicles. These changes correlated with uterine and vaginal atrophy. A No Observed Adverse Effect Level (NOAEL) was not identified. Intravenous administration of the lowest dose of aflibercept assessed in monkeys (3 mg per kg) resulted in systemic exposure (AUC) for free aflibercept that was approximately 1500 times higher than the systemic exposure observed in adult patients after an intravitreal dose of 2 mg. All changes were reversible within 20 weeks after cessation of treatment.

13.2 Animal Toxicology and/or Pharmacology

Erosions and ulcerations of the respiratory epithelium in nasal turbinates in monkeys treated with aflibercept intravitreally were observed at intravitreal doses of 2 or 4 mg per eye. At the NOAEL of 0.5 mg per eye in monkeys, the systemic exposure (AUC) was 56 times higher than the exposure observed in adult patients after an intravitreal dose of 2 mg. Similar effects were not seen in other clinical studies [see Clinical Studies (14)].

14 CLINICAL STUDIES

14.1 Neovascular (Wet) Age-Related Macular Degeneration (AMD)

The safety and efficacy of aflibercept were assessed in two randomized, multi-center, double-masked, active-controlled studies in patients with wet AMD. A total of 2412 patients were treated and evaluable for efficacy (1817 with aflibercept) in the two studies (VIEW1 and VIEW2). In each study, up to week 52, patients were randomly assigned in a 1:1:1:1 ratio to 1 of 4 dosing regimens: 1) aflibercept administered 2 mg every 8 weeks following 3 initial monthly doses (aflibercept 2Q8); 2) aflibercept administered 2 mg every 4 weeks (aflibercept 2Q4); 3) aflibercept 0.5 mg administered every 4 weeks (aflibercept 0.5Q4); and 4) ranibizumab administered 0.5 mg every 4 weeks (ranibizumab 0.5 mg Q4). Protocol-specified visits occurred every 28±3 days. Patient ages ranged from 49 to 99 years with a mean of 76 years.

In both studies, the primary efficacy endpoint was the proportion of patients who maintained vision, defined as losing fewer than 15 letters of visual acuity at week 52 compared to baseline. Both aflibercept 2Q8 and aflibercept 2Q4 groups were shown to have efficacy that was clinically equivalent to the ranibizumab 0.5 mg Q4 group in year 1.

Detailed results from the analysis of the VIEW1 and VIEW2 studies are shown in Table 4 and Figure 13 below.

Table 4: Efficacy Outcomes at Week 52 (Full Analysis Set with LOCF) in VIEW1 and VIEW2 Studies

 | VIEW 1 |  |  |  | VIEW 2
 | Aflibercept 2 mg Q8 weeksa | Aflibercept 2 mg Q4 weeks | ranibizu-mab 0.5 mg Q4 weeks | Aflibercept 2 mg Q8 weeksa |  | Aflibercept 2 mg Q4 weeks | ranibizu-mab 0.5 mg Q4 weeks
 | N=301 | N=304 | N=304 | N=306 |  | N=309 | N=291
Efficacy Outcomes
Proportion of patients who maintained visual acuity (%) (<15 letters of BCVA loss) | 94% | 95% | 94% | 95% |  | 95% | 95%
Differenceb (%) (95.1% CI) | 0.6 (-3.2, 4.4) | 1.3 (-2.4, 5.0) |  | 0.6 (-2.9, 4.0) |  | -0.3 (-4.0, 3.3)
Mean change in BCVA as measured by ETDRS letter score from Baseline | 7.9 | 10.9 | 8.1 | 8.9 |  | 7.6 | 9.4
Differenceb in LS mean (95.1% CI) | 0.3 (-2.0, 2.5) | 3.2 (0.9, 5.4) |  | -0.9 (-3.1, 1.3) |  | -2.0 (-4.1, 0.2)
Number of patients who gained at least 15 letters of vision from Baseline (%) | 92 (31%) | 114 (38%) | 94 (31%) | 96 (31%) |  | 91 (29%) | 99 (34%)
Differenceb (%) (95.1% CI) | -0.4 (-7.7, 7.0) | 6.6 (-1.0, 14.1) |  | -2.6 (-10.2, 4.9) |  | -4.6 (-12.1, 2.9)

BCVA = Best Corrected Visual Acuity; CI = Confidence Interval; ETDRS = Early Treatment Diabetic Retinopathy Study; LOCF = Last Observation Carried Forward (baseline values are not carried forward); 95.1% confidence intervals were presented to adjust for safety assessment conducted during the study

a After treatment initiation with 3 monthly doses

b Aflibercept group minus the ranibizumab group

Treatment effects in evaluable subgroups (e.g., age, gender, race, baseline visual acuity) in each study were in general consistent with the results in the overall populations.

Figure 13: Mean Change in Visual Acuity from Baseline to Week 96* in VIEW1 and VIEW2 Studies

*Patient dosing schedules were individualized from weeks 52 to 96 using a modified 12-week dosing regimen.

VIEW1 and VIEW2 studies were both 96 weeks in duration. However after 52 weeks patients no longer followed a fixed dosing schedule. Between week 52 and week 96, patients continued to receive the drug and dosage strength to which they were initially randomized on a modified 12 week dosing schedule (doses at least every 12 weeks and additional doses as needed). Therefore, during the second year of these studies there was no active control comparison arm.

14.2 Macular Edema Following Central Retinal Vein Occlusion (CRVO)

The safety and efficacy of aflibercept were assessed in two randomized, multi-center, double-masked, sham-controlled studies in patients with macular edema following CRVO. A total of 358 patients were treated and evaluable for efficacy (217 with aflibercept) in the two studies (COPERNICUS and GALILEO). In both studies, patients were randomly assigned in a 3:2 ratio to either 2 mg aflibercept administered every 4 weeks (2Q4), or sham injections (control group) administered every 4 weeks for a total of 6 injections. Protocol-specified visits occurred every 28±7 days. Patient ages ranged from 22 to 89 years with a mean of 64 years.

In both studies, the primary efficacy endpoint was the proportion of patients who gained at least 15 letters in BCVA compared to baseline. At week 24, the aflibercept 2 mg Q4 group was superior to the control group for the primary endpoint.

Results from the analysis of the COPERNICUS and GALILEO studies are shown in Table 5 and Figure 14 below.

Table 5: Efficacy Outcomes at Week 24 (Full Analysis Set with LOCF) in COPERNICUS and GALILEO Studies

 | COPERNICUS |  | GALILEO
 | Control | Aflibercept 2 mg Q4 weeks | Control | Aflibercept 2 mg Q4 weeks
 | N=73 | N=114 | N=68 | N=103
Efficacy Outcomes
Proportion of patients who gained at least 15 letters in BCVA from Baseline (%) | 12% | 56% | 22% | 60%
Weighted Difference a, b (%) (95.1% CI) |  | 44.8%c (32.9, 56.6) |  | 38.3%c (24.4, 52.1)
Mean change in BCVA as measured by ETDRS letter score from Baseline (SD) | -4.0 (18.0) | 17.3 (12.8) | 3.3 (14.1) | 18.0 (12.2)
Difference in LS meana, d (95.1% CI) |  | 21.7c (17.3, 26.1) |  | 14.7c (10.7, 18.7)

a Difference is Aflibercept 2 mg Q4 weeks minus Control

b Difference and CI are calculated using Cochran-Mantel-Haenszel (CMH) test adjusted for baseline factors; 95.1% confidence intervals were presented to adjust for the multiple assessments conducted during the study

c p<0.01 compared with Control

d LS mean and CI based on an ANCOVA model

Figure 14: Mean Change in BCVA as Measured by ETDRS Letter Score from Baseline to Week 24 in COPERNICUS and GALILEO Studies

Treatment effects in evaluable subgroups (e.g., age, gender, race, baseline visual acuity, retinal perfusion status, and CRVO duration) in each study and in the combined analysis were in general consistent with the results in the overall populations.

14.3 Macular Edema Following Branch Retinal Vein Occlusion (BRVO)

The safety and efficacy of aflibercept were assessed in a 24-week, randomized, multi-center, double-masked, controlled study in patients with macular edema following BRVO. A total of 181 patients were treated and evaluable for efficacy (91 with aflibercept) in the VIBRANT study. In the study, patients were randomly assigned in a 1:1 ratio to either 2 mg aflibercept administered every 4 weeks (2Q4) or laser photocoagulation administered at baseline and subsequently as needed (control group). Protocol-specified visits occurred every 28±7 days. Patient ages ranged from 42 to 94 years with a mean of 65 years.

In the VIBRANT study, the primary efficacy endpoint was the proportion of patients who gained at least 15 letters in BCVA at week 24 compared to baseline. At week 24, the aflibercept 2 mg Q4 group was superior to the control group for the primary endpoint.

Detailed results from the analysis of the VIBRANT study are shown in Table 6 and Figure 15 below.

Table 6: Efficacy Outcomes at Week 24 (Full Analysis Set with LOCF) in VIBRANT Study

 | VIBRANT
 | Control | Aflibercept 2 mg Q4 weeks
 | N=90 | N=91
Efficacy Outcomes
Proportion of patients who gained at least 15 letters in BCVA from Baseline (%) | 26.7% | 52.7%
Weighted Differencea, b (%) (95% CI) |  | 26.6%c (13.0, 40.1)
Mean change in BCVA as measured by ETDRS letter score from Baseline (SD) | 6.9 (12.9) | 17.0 (11.9)
Difference in LS mean a, d (95% CI) |  | 10.5c (7.1, 14.0)

a Difference is Aflibercept 2 mg Q4 weeks minus Control

b Difference and CI are calculated using Mantel-Haenszel weighting scheme adjusted for region (North America vs. Japan) and baseline BCVA category (> 20/200 and ≤ 20/200)

c p<0.01 compared with Control

d LS mean and CI based on an ANCOVA model

Figure 15: Mean Change in BCVA as Measured by ETDRS Letter Score from Baseline to Week 24 in VIBRANT Study

Treatment effects in evaluable subgroups (e.g., age, gender, and baseline retinal perfusion status) in the study were in general consistent with the results in the overall populations.

14.4 Diabetic Macular Edema (DME)

The safety and efficacy of aflibercept were assessed in two randomized, multi-center, double-masked, controlled studies in patients with DME. A total of 862 randomized and treated patients were evaluable for efficacy. Protocol-specified visits occurred every 28±7 days. Patient ages ranged from 23 to 87 years with a mean of 63 years.

Of those, 576 were randomized to aflibercept groups in the two studies (VIVID and VISTA). In each study, patients were randomly assigned in a 1:1:1 ratio to 1 of 3 dosing regimens:
1) aflibercept administered 2 mg every 8 weeks following 5 initial monthly injections (aflibercept 2Q8); 2) aflibercept administered 2 mg every 4 weeks (aflibercept 2Q4); and 3) macular laser photocoagulation (at baseline and then as needed). Beginning at week 24, patients meeting a pre‑specified threshold of vision loss were eligible to receive additional treatment: patients in the aflibercept groups could receive laser and patients in the laser group could receive aflibercept.

In both studies, the primary efficacy endpoint was the mean change from baseline in BCVA at week 52 as measured by ETDRS letter score. Efficacy of both aflibercept 2Q8 and aflibercept 2Q4 groups was statistically superior to the control group. This statistically superior improvement in BCVA was maintained at week 100 in both studies.

Results from the analysis of the VIVID and VISTA studies are shown in Table 7 and Figure 16 below.

Table 7: Efficacy Outcomes at Weeks 52 and 100 (Full Analysis Set with LOCF) in VIVID and VISTA Studies

 | VIVID |  |  | VISTA
 | Aflibercept 2 mg Q8 weeksa | Aflibercept 2 mg Q4 weeks | Control | Aflibercept 2 mg Q8 weeksa | Aflibercept 2 mg Q4 weeks | Control
Full Analysis Set | N=135 | N=136 | N=132 | N=151 | N=154 | N=154
Efficacy Outcomes at Week 52
Mean change in BCVA as measured by ETDRS letter score from Baseline (SD) | 10.7 (9.3) | 10.5 (9.6) | 1.2 (10.6) | 10.7 (8.2) | 12.5 (9.5) | 0.2 (12.5)
Differenceb, c in LS mean (97.5% CI) | 9.1d (6.3, 11.8) | 9.3d (6.5, 12.0) |  | 10.5d (7.7, 13.2) | 12.2d (9.4, 15.0)
Proportion of patients who gained at least 15 letters in BCVA from Baseline (%) | 33.3% | 32.4% | 9.1% | 31.1% | 41.6% | 7.8%
Adjusted Differencec, e (%) (97.5% CI) | 24.2d (13.5, 34.9) | 23.3d (12.6, 33.9) |  | 23.3d (13.5, 33.1) | 34.2d (24.1, 44.4)
Efficacy Outcomes at Week 100
Mean change in BCVA as measured by ETDRS letter score from Baseline (SD) | 9.4 (10.5) | 11.4 (11.2) | 0.7 (11.8) | 11.1 (10.7) | 11.5 (13.8) | 0.9 (13.9)
Differenceb,c in LS mean (97.5% CI) | 8.2d (5.2, 11.3) | 10.7d (7.6, 13.8) |  | 10.1d (7.0, 13.3) | 10.6d (7.1, 14.2)
Proportion of patients who gained at least 15 letters in BCVA from Baseline (%) | 31.1% | 38.2% | 12.1% | 33.1% | 38.3% | 13.0%
Adjusted Differencec, e (%) (97.5% CI) | 19.0d (8.0, 29.9) | 26.1d (14.8, 37.5) |  | 20.1d (9.6, 30.6) | 25.8d (15.1, 36.6)

a After treatment initiation with 5 monthly injections

b LS mean and CI based on an ANCOVA model with baseline BCVA measurement as a covariate and a factor for treatment group. Additionally, protocol specified stratification factors were included in the model

c Difference is Aflibercept group minus Control group

d p<0.01 compared with Control

e Difference with confidence interval (CI) and statistical test is calculated using Mantel-Haenszel weighting scheme adjusted by protocol specified stratification factors

Figure 16: Mean Change in BCVA as Measured by ETDRS Letter Score from Baseline to Week 100 in VIVID and VISTA Studies

Treatment effects in the subgroup of patients who had previously been treated with a VEGF inhibitor prior to study participation were similar to those seen in patients who were VEGF inhibitor naïve prior to study participation.

Treatment effects in evaluable subgroups (e.g., age, gender, race, baseline HbA1c, baseline visual acuity, prior anti-VEGF therapy) in each study were in general consistent with the results in the overall populations.

14.5 Diabetic Retinopathy (DR)

Efficacy and safety data of aflibercept in diabetic retinopathy (DR) are derived from the VIVID, VISTA, and PANORAMA studies.

VIVID AND VISTA

In the VIVID and VISTA studies, an efficacy outcome was the change in the Early Treatment Diabetic Retinopathy Study (ETDRS) Diabetic Retinopathy Severity Scale (ETDRS-DRSS). The ETDRS-DRSS score was assessed at baseline and approximately every 6 months thereafter for the duration of the studies [see Clinical Studies (14.4)].

All enrolled patients had DR and DME at baseline. The majority of patients enrolled in these studies (77%) had moderate-to-severe nonproliferative diabetic retinopathy (NPDR) based on the ETDRS-DRSS. At week 100, the proportion of patients improving by at least 2 steps on the ETDRS-DRSS was significantly greater in both aflibercept treatment groups (2Q4 and 2Q8) when compared to the control group.

Results from the analysis of ETDRS-DRSS at week 100 in the VIVID and VISTA studies are shown in Table 8 below.

Table 8: Proportion of Patients Who Achieved a ≥2-Step Improvement from Baseline in the ETDRS-DRSS Score at Week 100 in VIVID and VISTA Studies

 | VIVID |  |  | VISTA
 | Aflibercept 2 mg Q8 weeks a | Aflibercept 2 mg Q4 weeks | Control | Aflibercept 2 mg Q8 weeksa | Aflibercept 2 mg Q4 weeks | Control
Evaluable Patientsb | N=101 | N=97 | N=99 | N=148 | N=153 | N=150
Number of patients with a ≥2-step improvement on ETDRS-DRSS from Baseline (%) | 32 (32%) | 27 (28%) | 7 (7%) | 56 (38%) | 58 (38%) | 24 (16%)
Differencec,d (%) (97.5% CI) | 24%e (12, 36) | 21%e (9, 33) |  | 22%e (11, 33) | 22%e (11, 33)

Non-gradable post-baseline ETDRS-DRSS values were treated as missing and were imputed using the last gradable ETDRS-DRSS values (including baseline values if all post-baseline values were missing or non-gradable)

a After treatment initiation with 5 monthly injections

b The number of evaluable patients included all patients who had valid ETDRS-DRSS data at baseline

c Difference with confidence interval (CI) was calculated using Mantel-Haenszel weighting scheme adjusted by protocol specified stratification factors

d Difference is Aflibercept minus Control group

e p<0.01 compared with Control

Results of the evaluable subgroups (e.g., age, gender, race, baseline HbA1c, baseline visual acuity) on the proportion of patients who achieved a ≥2-step improvement on the ETDRS-DRSS from baseline to week 100 were, in general, consistent with those in the overall population.

PANORAMA

The PANORAMA study assessed the safety and efficacy of aflibercept in a randomized, multi-center, double-masked, controlled study in patients with moderately severe to severe nonproliferative diabetic retinopathy (NPDR) (ETDRS-DRSS of 47 or 53), without central-involved DME (CI-DME). A total of 402 randomized patients were evaluable for efficacy. Protocol-specified visits occurred every 28±7 days for the first 5 visits, then every 8 weeks (56±7 days). Patient ages ranged from 25 to 85 years with a mean of 55.7 years.

Patients were randomly assigned in a 1:1:1 ratio to 1 of 3 dosing regimens: 1) 3 initial monthly aflibercept 2 mg injections followed by one injection after 8 weeks and then one injection every 16 weeks (aflibercept 2Q16); 2) 5 monthly aflibercept 2 mg injections followed by one injection every 8 weeks (aflibercept 2Q8); and 3) sham treatment.

The primary efficacy endpoint was the proportion of patients who improved by ≥2 steps on the DRSS from baseline to week 24 in the combined aflibercept groups and at week 52 in the 2Q16 and 2Q8 groups individually versus sham. A key secondary endpoint was the proportion of patients developing the composite endpoint of proliferative diabetic retinopathy or anterior segment neovascularization through week 52.

At week 52, efficacy in the 2Q16 and 2Q8 groups was superior to the sham group (see Table 9 and Table 10). The proportion of patients with a ≥2-step improvement over time is shown in Figure 17.

Table 9: Proportion of Patients Who Achieved a ≥2-Step Improvement from Baseline in the ETDRS-DRSS Score at Weeks 24 and 52 in PANORAMA

 | PANORAMA
 | Week 24 |  | Week 52
 | Aflibercept Combined | Control (sham) | Aflibercept 2Q16 | Aflibercept 2Q8 | Control (sham)
Full Analysis Set | N=269 | N=133 | N=135 | N=134 | N=133
Proportion of patients with a ≥2-step improvement on ETDRS-DRSS from Baseline (%) | 58% | 6% | 65% | 80% | 15%
Adjusted Differencea (%) (95% CI)b | 52%c (45, 60) |  | 50%c (40, 60) | 65%c (56, 74)

Non-gradable post-baseline ETDRS-DRSS values were treated as missing and were imputed using the last gradable ETDRS-DRSS values (including baseline values if all post-baseline values were missing or non-gradable)

a Difference is Aflibercept group minus sham

b Difference with CI was calculated using the Mantel-Haenszel weighting scheme adjusted by baseline DRSS stratification variable

c p<0.01 compared with Control. p-value was calculated using a 2-sided Cochran-Mantel-Haenszel test adjusted by baseline DRSS stratification variable

Figure 17: Proportion of Patients Who Achieved a ≥2-Step Improvement from Baseline in the ETDRS-DRSS Score Through Week 52 in PANORAMA

Table 10: Effect of Aflibercept on Worsening of Diabetic Retinopathy in PANORAMA through Week 52

 | Aflibercept 2Q16 | Aflibercept 2Q8 | Control (sham)
Full Analysis Set | N=135 | N=134 | N=133
Composite Endpoint of Developing PDR or ASNVa
Event Rateb | 4.0%d | 2.4%d | 20.1%
Hazard Ratio | 0.15 | 0.12
Development of Proliferative Diabetic Retinopathyc
Event Rateb | 1.6%d | 0.0%d | 11.9%
Hazard Ratio | 0.11 | 0.00

PDR = Proliferative Diabetic Retinopathy; ASNV = Anterior Segment Neovascularization

a As diagnosed by either the Reading Center or Investigator through week 52

b Estimated using Kaplan-Meier method

c Defined as ≥2-step worsening on the ETDRS-DRSS score through week 52

d p<0.01 compared with Control

16 HOW SUPPLIED/STORAGE AND HANDLING

16.1 How Supplied

Each pre-filled syringe or vial is for single eye use only. Discard unused portion.

AHZANTIVE (aflibercept-mrbb) injection is a clear, colorless to pale yellow solution and is supplied in the following presentation [see Dosage and Administration (2.1), (2.6), (2.7) and (2.8)].

NDC Number | Carton Type | Carton Contents
85006-8092-1 | Pre-filled Syringe | one blister pack containing one AHZANTIVE 2 mg (0.05 mL of a 40 mg/mL solution) sterile, single‑dose pre-filled syringe; one Prescribing Information
85006-2908-1 | Vial Only | one AHZANTIVE 2 mg (0.05 mL of a 40 mg/mL solution) single-dose glass vial; one Prescribing Information

The AHZANTIVE pre-filled syringe cap and plunger are not made with natural rubber latex.

The AHZANTIVE vial stopper is not made with natural rubber latex.

16.2 Storage and Handling

Refrigerate AHZANTIVE at 2°C to 8ºC (36°F to 46ºF). Do not freeze. Do not use beyond the date stamped on the carton and container label. Store in the original carton until time of use to protect from light.

17 PATIENT COUNSELING INFORMATION

In the days following AHZANTIVE administration, patients are at risk of developing endophthalmitis, retinal detachment, or retinal vasculitis with or without occlusion. If the eye becomes red, sensitive to light, painful, or develops a change in vision, advise patients and/or caregivers to seek immediate care from an ophthalmologist [see Warnings and Precautions (5.1)].

Patients may experience temporary visual disturbances after an intravitreal injection with AHZANTIVE and the associated eye examinations [see Adverse Reactions (6)]. Advise patients not to drive or use machinery until visual function has recovered sufficiently.